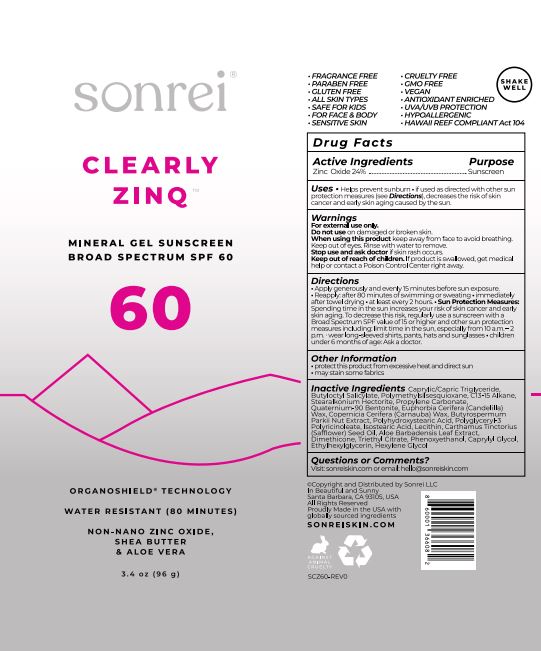 DRUG LABEL: Clearly Zinq Mineral Gel Sunscreen BS SPF 60
NDC: 62742-4236 | Form: GEL
Manufacturer: Allure Labs
Category: otc | Type: HUMAN OTC DRUG LABEL
Date: 20231204

ACTIVE INGREDIENTS: ZINC OXIDE 24 g/100 g
INACTIVE INGREDIENTS: QUATERNIUM-90 BENTONITE; POLYGLYCERYL-3 PENTARICINOLEATE; ALOE VERA LEAF; CAPRYLYL GLYCOL; MEDIUM-CHAIN TRIGLYCERIDES; BUTYLOCTYL SALICYLATE; C13-15 ALKANE; STEARALKONIUM HECTORITE; CANDELILLA WAX; PROPYLENE CARBONATE; CARNAUBA WAX; SAFFLOWER OIL; DIMETHICONE; TRIETHYL CITRATE; ETHYLHEXYLGLYCERIN; HEXYLENE GLYCOL; SHEANUT; ISOSTEARIC ACID; PHENOXYETHANOL; POLYMETHYLSILSESQUIOXANE/TRIMETHYLSILOXYSILICATE; POLYHYDROXYSTEARIC ACID (2300 MW); LECITHIN, SOYBEAN

Drug Facts

Active ingredient,

Zinc Oxide – 24 %

Purpose; Sunscreen

INDICATIONS AND USAGE

Uses. Helps prevent sunburn.

If used as directed with other sun protection measures (see Direction), decreases the risk of skin cancer and early skin aging caused by the sun.

Warnings

For external use only.

Do not use on damaged or broken skin.

When using this product keep out of eye.Rinse with water to remove.

Stop use and ask doctor if skin rash occurs.

Keep out of reach of children, If product is swallowed, get medical help or contact a poison control center right away.

Directions.

Apply generously and evenly 15 minutes before sun exposure.

Reapply: after 80 minutes of swimming or sweating.

Immediately after towel drying. At least every 2 hours. Sun Protection Measures: Spending time the sun increases your risk of skin cancer and early skin aging. To decrease this risk, regularly use of sunscreen with a broad spectrum SPF value of 15 or higher and other sun protection measures including: limit time in the sun, especially from 10 a.m. – 2 p.m. wear long-sleeved shirts, pants, hats and sunglasses. Children under 6 months of age: Ask a doctor.

Other information.

Protect this product from excessive heat an direct sun.

May stain some fabrics.

Inactive ingredient:

Caprylic/Capric Triglyceride, Butyloctyl Salicylate, Polymethylsilsesquioxane, C13-15Alkane, stearalkonium Hectorite,Propylene Carbonate, Quaternium-90 Bentonite, Euphorbia Cerifera (Candelilla) Wax, Copernicia Cerifera (Carnauba) Wax, Bytyrospermum Parkii Nut Extract, Polyhydroxystearic Acid, Polyglyceryl-3 Polyricinoleate, Isostearic Acid, Lecithin, Carthamus Tinctorius (Safflower) Seed Oil, Aloe Barbandensis Leaf Extract, Dimethicon, Triethyl Citrate, Phenoxyethanol, Caprylyl Glycol, Ethylhexylglycerin, Hexylene Glycol.